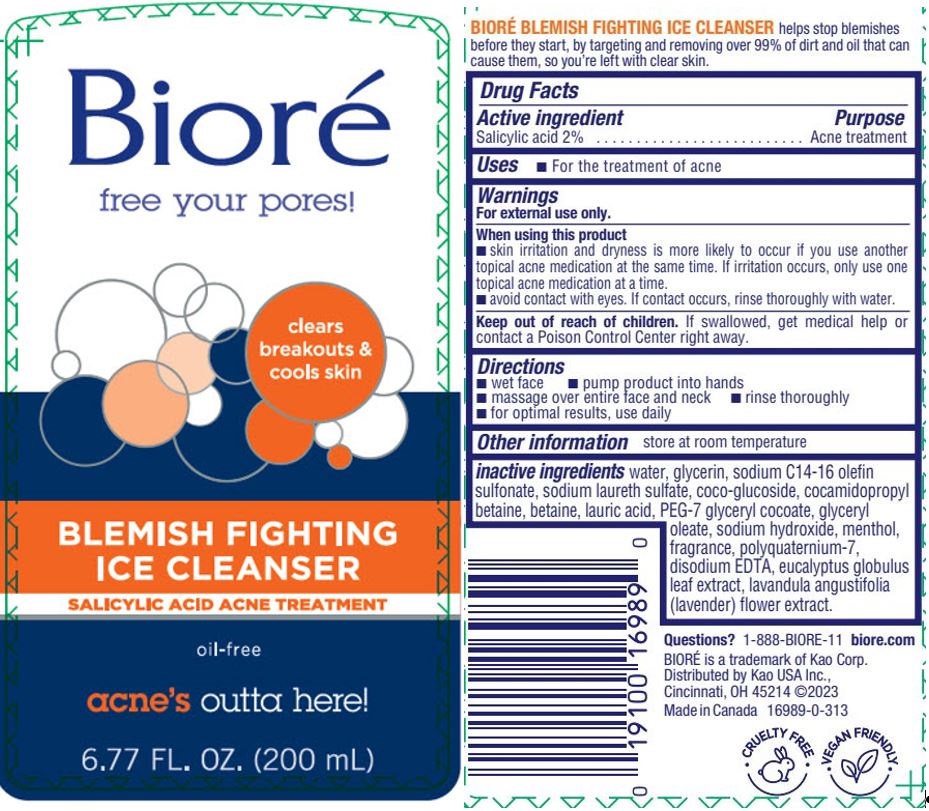 DRUG LABEL: Biore
NDC: 10596-159 | Form: LIQUID
Manufacturer: Kao USA Inc.
Category: otc | Type: HUMAN OTC DRUG LABEL
Date: 20250101

ACTIVE INGREDIENTS: SALICYLIC ACID 4.3 g/200 mL
INACTIVE INGREDIENTS: WATER; GLYCERIN; SODIUM C14-16 OLEFIN SULFONATE; SODIUM LAURETH SULFATE; COCO GLUCOSIDE; COCAMIDOPROPYL BETAINE; LAURIC ACID; BETAINE; LAVANDULA ANGUSTIFOLIA FLOWER; EUCALYPTUS GLOBULUS LEAF; PEG-7 GLYCERYL COCOATE; GLYCERYL OLEATE; SODIUM HYDROXIDE; POLYQUATERNIUM-7 (70/30 ACRYLAMIDE/DADMAC; 1600 KD); EDETATE DISODIUM; MENTHOL

Biore Blemish Fighting Ice Cleanser

Drug Facts

Active ingredient

Salicylic acid 2%

Purpose

Acne treatment

Uses

- For the treatment of acne

Warnings

For external use only

When using this product

- skin irritation and dryness is more likely to occur if you use another topical acne medication at the same time. If irritation occurs, only use one topical acne medication at a time.
- avoid contact with eyes. If contact occurs, rinse thoroughly with water.

Keep out of reach of children. If swallowed, get medical help or contact a Poison Control Center right away.

Directions

- wet face
- pump product into hands
- massage over entire face and neck
- rinse thoroughly
- for optimal results, use daily

STORAGE AND HANDLING

Other informationstore at room temperature

INACTIVE INGREDIENT

Inactive ingredientswater, glycerin, sodium C14-16 olefin sulfonate, sodium laureth sulfate, coco-glucoside, cocamidipropyl betaine, betaine, lauric acid, PEG-7 glyceryl cocoate, glyceryl oleate, sodium hydroxide, menthol, fragrance, polyquaternium-7, disodium EDTA, eucalyptus globulus leaf extract, lavandula angustifolia (lavender) flower extract.

Questions? 1-888-BIORE-11

www.biore.com

BIORE is a trademark of Kao Corp.

Distributed by Kao USA Inc.
Cincinnati, OH 45214 ©2023
Made in Canada

PACKAGE LABEL

Biore

free your pores!

clears breakouts and cools skin

BLEMISH FIGHTING ICE CLEANSER

SALICYLIC ACID ACNE TREATMENT

oil-free

acne's outta here!

6.77 FL OZ (200 mL)